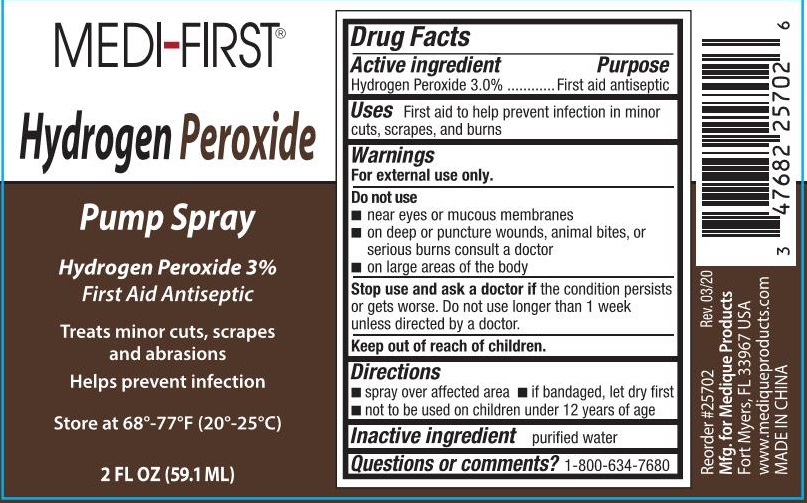 DRUG LABEL: Medi-First Hydrogen Peroxide
NDC: 47682-275 | Form: SPRAY
Manufacturer: Unifirst First Aid Corporation
Category: otc | Type: HUMAN OTC DRUG LABEL
Date: 20250908

ACTIVE INGREDIENTS: HYDROGEN PEROXIDE 43.275 g/1 L
INACTIVE INGREDIENTS: WATER

Medi-First Hydrogen Peroxide Spray

Active ingredients

Hydrogen Peroxide 3.0%

Purpose

First aid antiseptic

Uses

First aid to help prevent infection in minor cuts, scrapes, and burns

Warnings

For external use only.

Do not use

- near eyes or mucus membranes
- on deep or puncture wounds, aniaml bites, or serious burns consult a doctor
- on large areas of the body

Stop use and ask a doctor if condition persists or gets worse. Do not use longer than 1 week unless directed by a doctor.

Keep out of reach of children.

Directions

- spray over affected area
- if bandaged, let dry first
- not to be used on children under 12 years of age

Inactive ingredient

purified water

Questions or comments? 1-800-634-7680

Medi-First Hydogen Peroxide Spray Label

Medi-First®

Hydrogen Peroxide

Pump Spray

Hydrogen Peroxide 3%

First Aid Antiseptic

Treats minor cuts, scrapes and abrasions

Helps prevent infection

Store at 68°-77°F (20°-25°C)

2 FL OZ (59.1 ML)